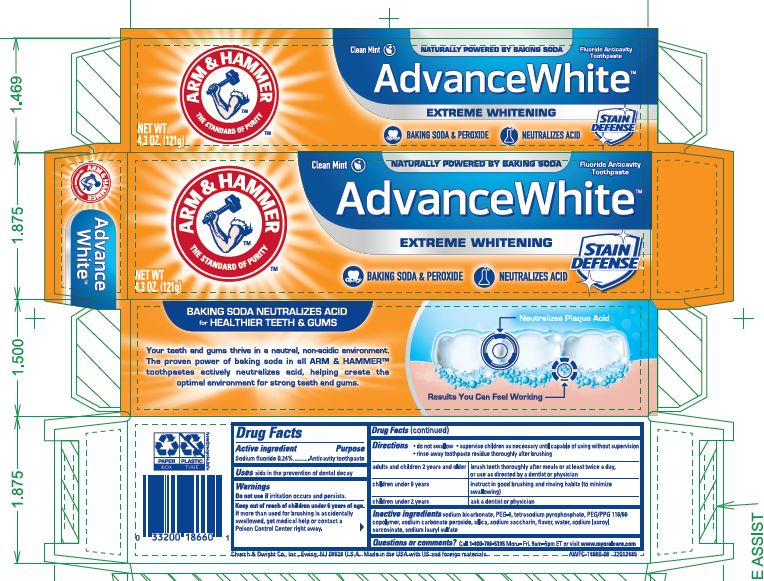 DRUG LABEL: Advance White Extreme Whitening
NDC: 10237-658 | Form: PASTE, DENTIFRICE
Manufacturer: Church & Dwight Co., Inc.
Category: otc | Type: HUMAN OTC DRUG LABEL
Date: 20251202

ACTIVE INGREDIENTS: SODIUM FLUORIDE 2.4 mg/1 g
INACTIVE INGREDIENTS: SODIUM BICARBONATE; POLYETHYLENE GLYCOL 400; POLOXALENE; SODIUM PERCARBONATE; SODIUM PYROPHOSPHATE; SILICON DIOXIDE; SACCHARIN SODIUM; WATER; SODIUM LAURYL SULFATE; SODIUM LAUROYL SARCOSINATE

Advance White Extreme Whitening Tartar Control

Active ingredients
Sodium fluoride (0.24%)

Purpose
Anticavity toothpaste

INDICATIONS AND USAGE

Use aids in the prevention of dental decay

Warnings
Do not use if irritation occurs and persists.

Keep out of reach of children under 6 years of age.
If more than used for brushing is accidentally swallowed, get medical help or contact a Poison Control Center right away.

DOSAGE AND ADMINISTRATION

Directions do not swallow supervise children as necessary until capable of using without supervision
rinse away toothpaste residue throughly after brushing

adults and children 2 years and older brush teeth thoroughly after meals or at least twice a day, or use as directed by a dentist or physician
children under 6 years instruct in good brushing and rinsing habits (to minimize swallowing)
children under 2 years ask a dentist or physician

INACTIVE INGREDIENT

Inactive ingredients sodium bicarbonate, PEG-8, tetrasodium pyrophosphate,PEG/PPG-116/66 copolymer, sodium carbonate peroxide, silica, sodium saccharin, flavor, water, sodium lauroyl sarcosinate, sodium lauryl sulfate

Questions or comments? Call 1-800-786-5135Monday-Friday 9am-5pm ET or visit www.myoralcare.com

Principal Display Panel

ARM AND HAMMER The Standard of Purity

Clean Mint NATURALLY POWERED BY BAKING SODA Fluoride Anticavity Toothpaste

AdvanceWhite

EXTREME WHITENING STAIN DEFENSE

BAKING SODA AND PEROXIDE NEUTRALIZES ACID

NET WT. 6.0 OZ. (170g)